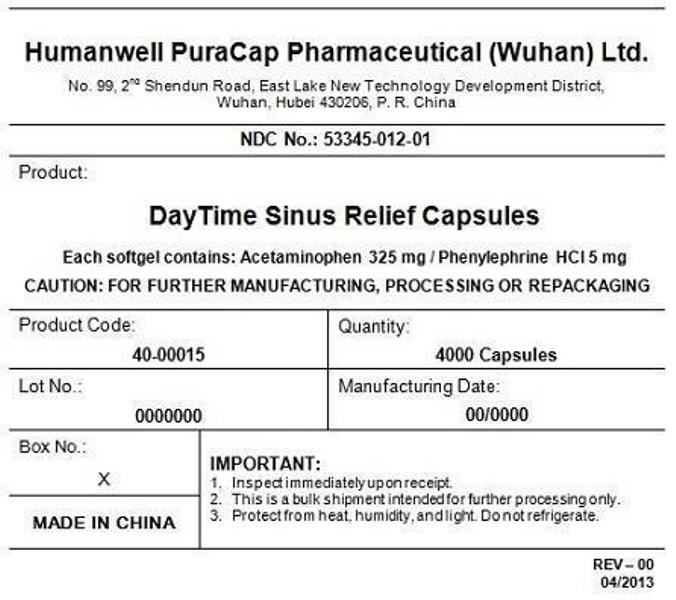 DRUG LABEL: DayTime Sinus Relief
NDC: 53345-012 | Form: CAPSULE, LIQUID FILLED
Manufacturer: Humanwell PuraCap Pharmaceutical (Wuhan), Ltd.
Category: otc | Type: HUMAN OTC DRUG LABEL
Date: 20241125

ACTIVE INGREDIENTS: ACETAMINOPHEN 325 mg/1 1; PHENYLEPHRINE HYDROCHLORIDE 5 mg/1 1
INACTIVE INGREDIENTS: FD&C YELLOW NO. 6; GELATIN; GLYCERIN; POLYETHYLENE GLYCOL, UNSPECIFIED; POVIDONE; PROPYLENE GLYCOL; WATER; SORBITOL; TITANIUM DIOXIDE

DayTime Sinus Relief capsule, liquid filled

Active ingredients (in each capsule)

Acetaminophen 325 mg

Phenylephrine HCl 5 mg

Purpose

Pain reliever

Nasal decongestant

Uses

temporarily relieves sinus symptoms:

- sinus pain
- headache
- nasal & sinus congestion

Warnings

Liver warning

This product contains acetaminophen. Severe liver damage may occur if you take

- more than 4 doses in 24 hours, which is the maximum daily amount
- with other drugs containing acetaminophen
- 3 or more alcoholic drinks daily while using this product

Do not use

- with any other drug containing acetaminophen (prescription or nonprescription). If you are not sure whether a drug contains acetaminophen, ask a doctor or pharmacist.
- if you are now taking a prescription monoamine oxidase inhibitor (MAOI) (certain drugs for depression, psychiatric, or emotional conditions, or Parkinson's disease), or for 2 weeks after stopping the MAOI drug. If you do not know if your prescription drug contains an MAOI, ask a doctor or pharmacist before taking this product.

Ask a doctor before use if you have

- liver disease
- heart disease
- thyroid disease
- diabetes
- high blood pressure
- trouble urinating due to enlarged prostate gland

Ask a doctor or pharmacist before use if you are taking the blood thinning drug warfarin.

When using this product, do not use more than directed.

Stop use and ask a doctor if

- redness or swelling is present
- you get nervous, dizzy or sleepless
- fever gets worse or lasts more than 3 days
- new symptoms occur
- symptoms do not get better within 7 days or are accompanied by a fever

PREGNANCY OR BREAST FEEDING

If pregnant or breast-feeding,ask a health professional before use.

Keep out of reach of children.

Overdose warning

Taking more than directed can cause serious health problems. In case of overdose, get medical help or contact a Poison Control Center right away. Quick medical attention is critical for adults & for children even if you do not notice any signs or symptoms.

Directions

- take only as directed - see Overdose warning
- do not exceed 4 doses per 24 hours

Adults & children 12 yrs & over | 2 softgels with water every 4 hrs
Children 4 to under 12 yrs | ask a doctor
children under 4 yrs | do not use

- when taking NIGHTTIME and DAYTIME products, carefully read each label to insure correct dosing

Other information

- store at room temperature 15°-30°C (59°-86°F)

Inactive ingredients

FD&C Yellow #6, gelatin, glycerin, polyethylene glycol, povidone, propylene glycol, purified water, sorbitol special, titanium dioxide

Manufactured by:
Humanwell PuraCap Pharmaceutical (Wuhan) Ltd.
Wuhan, Hubei
430206, China

PRINCIPAL DISPLAY PANEL - Shipping Label

DayTime Sinus Relief Capsules

Quantity : 4000 Capsules
NDC. No : 53345-012-01

IMPORTANT:

Inspect immediate upon receipt.
This is a bulk shipment intended for further processing only.
Protect from heat, humidity, and light. Do not refrigerate.

CAUTION : "FOR FURTHER MANUFACTURING, PROCESSING OR REPACKING"